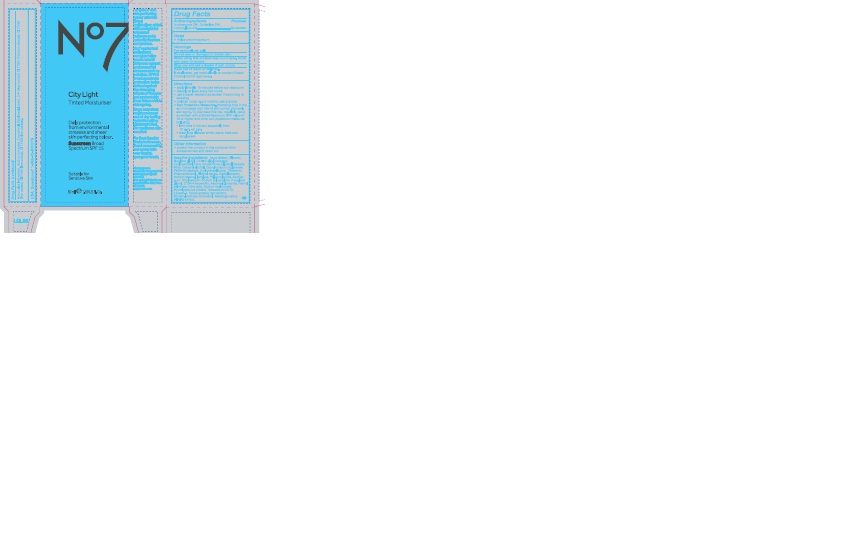 DRUG LABEL: No7 City Light Tinted Moisturiser Sunscreen Broad Spectrum SPF 15 Medium Dark
NDC: 61589-1923 | Form: CREAM
Manufacturer: BCM Cosmetique SAS
Category: otc | Type: HUMAN OTC DRUG LABEL
Date: 20161214

ACTIVE INGREDIENTS: AVOBENZONE 1.5 g/50 g; OCTISALATE 1 g/50 g; OCTOCRYLENE 2 g/50 g
INACTIVE INGREDIENTS: WATER; CYCLOMETHICONE 5; GLYCERIN; BUTYLENE GLYCOL; DIMETHICONE; GLYCERYL STEARATE SE; MICA; PEG-100 STEARATE; CYCLOMETHICONE 6; TRIBEHENIN; PHENOXYETHANOL; METHYLPARABEN; SODIUM STEAROYL LACTYLATE; ETHYLPARABEN; POLYACRYLAMIDE (10000 MW); XANTHAN GUM; SODIUM POLYACRYLATE (8000 MW); PROPYLENE GLYCOL; C13-14 ISOPARAFFIN; ASCORBYL GLUCOSIDE; CITRIC ACID ACETATE; TOCOPHEROL; VITAMIN A PALMITATE; ETIDRONATE TETRASODIUM; LAURETH-7; PANAX GINSENG ROOT OIL; DIMETHYLMETHOXY CHROMANOL; MEDICAGO SATIVA LEAF; MORUS ALBA LEAF; SODIUM BENZOATE; ETHYLHEXYLGLYCERIN; TITANIUM DIOXIDE; FERRIC OXIDE YELLOW; FERRIC OXIDE RED; FERROSOFERRIC OXIDE

No7 City Light Tinted Moisturiser Sunscreen Broad Spectrum SPF 15 Medium Dark

Carton Active Ingredients Section

Active Ingredients

Avobenzone 3%, Octisalate 2%, Octocrylene 4%

Uses

Uses - helps prevent sunburn

Warnings

For external use only

Do not use on damaged or broken skin

When using this product keep out of eyes. Rinse with water to remove

Ask a doctor

Stop use and ask a doctor if rash occurs.

Keep out of reach of children. If swallowed, get medical help or contact a Poison Control Center right away.

Directions

Directions for suncreen use

apply liberally 15 minutes before sun exposure

reapply at least every 2 hours

use a water resistant sunscreen if swimming or sweating

children under 6 months of age: Ask a doctor

Sun Protection Measures. Spending time in the sun increases your risk of skin cancer and early skin aging. To decrease this risk, regularly use a sunscreen with a Broad Spectrum SPF value of 15 or higher and other sun protection measures including:

limit time in the sun, especially from 10 a.m. - 2 p.m.

wear long-sleeved shirts, pants, hats, and sunglasses

Other information

Protect the product in this container from excessive heat and direct sun

Inactive ingredients

Aqua(Water), Glycerin, Butylene glycol, C12-15 alkyl benzoate, Cyclopentasiloxane, Dimethicone, Glyceryl stearate, Mica, Cetearyl alcohol, Caprylic/capric triglyceride, PEG-100 stearate, Cyclohexasiloxane, Tribehenin, Phenoxyethanol, Alcohol denat., Methylparaben, Sodium stearoyl lactylate, Polyacrylamide, Xanthan gum, Ethylparaben, Sodium polyacrylate, Propylene glycol, C13-14 isoparaffin, Ascorbyl glucoside, Retinyl palmitate, Citric acid, Sodium hyaluronate, Hydrolyzed rice protein, Tetrasodium EDTA, Laureth-7, Panax ginseng root extract, Dimethylmethoxy chromanol, Medicago sativa (Alfalfa) extract, Morus alba leaf extract, Sodium benzoate, Tocopherol, Ethylhexylglycerin, CI 77891(Titanium dioxide) CI 77492 (Iron oxides) CI 77491 (Iron oxides) CI 77499 (Iron oxides)

Description

No7 City Light

Tinted Moisturiser Sunscreen Broad Spectrum SPF 15

Daily protection from environmental stresses and sheer skin perfcting colour.

Suitable for Sensitive Skin

50ml e 1.69 US Fl.Oz

Information

Made in France

The Boots Company PLC

Nottingham England

NG2 3AA

Dist. in the USA by Boots

Retail USA Inc. New York

NY 10005

www.boots.com

active ingredients

No7 City Light Tinted Moisturiser Sunscreen Broad Spectrum SPF 15

50ml e 1.69 US Fl.Oz.

Active ingredients: Avobenzone 3%, Octisalate 2%, Octocrylene 4%

Description

Achieve sheer, skin perfecting colour with this tinted moisturiser, which diffuses light for enhanced radiance and a naturally flawless complexion

No7's patented antioxidant complex helps boost natural defences against environmental stresses such as pollution. SPF 15 broad spectrum protection helps defend against the damaging effects of the sun and protect skin from future visible skin ageing.

Gives an instant moisture boost and all day lasting hydration with a lightweight feel, for maximum skin comfort.

For Best Results: Shake before use. Blend on smoothly and evenly with your fingers, sponge or brush.